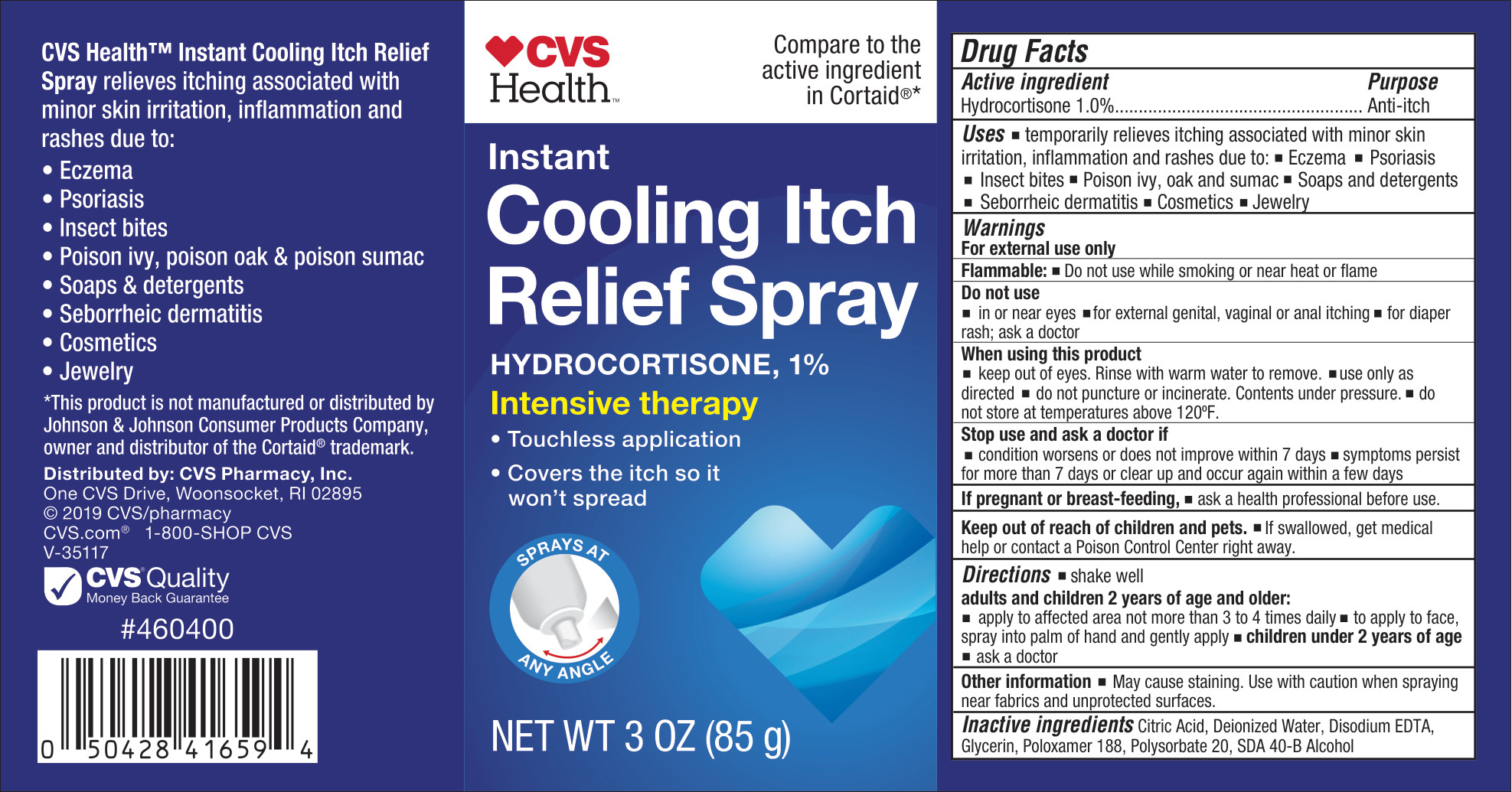 DRUG LABEL: Instant Cooling Itch Relief
NDC: 51316-388 | Form: SPRAY
Manufacturer: CVS Pharmacy
Category: otc | Type: HUMAN OTC DRUG LABEL
Date: 20251219

ACTIVE INGREDIENTS: HYDROCORTISONE 10 mg/1 g
INACTIVE INGREDIENTS: POLOXAMER 188; EDETATE DISODIUM; ALCOHOL; CITRIC ACID; GLYCERIN; WATER; POLYSORBATE 20

CVS Instant Cooling Itch Relief Spray

Active ingredient

Hydrocortisone 1%

Purpose

Anti-itch

Uses

temporarily relieves itching associated with minor skin irritation, inflammation and rashes due to:

- eczema
- psoriasis
- insect bites
- poison ivy, oak, and sumac
- soaps and detergents
- seborrheic dermatitis
- cosmetics
- jewelry

Warnings

For external use only.

Flammable: Do not use while smoking or near heat or flame

Do not use

- in or near eyes
- for external genital, vaginal or anal itching
- for diaper rash; ask a doctor

Do not use

- in or near eyes
- for external genital, vaginal or anal itching
- for diaper rash; ask a doctor

When using this product

- keep out of eyes. Rinse with warm water to remove.
- use only as directed
- do not puncture or incinerate. Contents under pressure.
- do not store at temperatures above 120 °F

Stop use and ask a doctor if

- condition worsens or does not improve within 7 days
- symptoms persist for more than 7 days or clear up and occur again within a few days

If pregnant or breast-feeding

ask a health professional before use.

Keep out of reach of children and pets.

If swallowed, get medical help or contact a Poison Control Center right away.

Directions

- shake well
- adults and children 2 years of age and older:
  - apply to affected area, not more than 3 to 4 times daily
  - to apply to face, spray into palm of hand and gently apply
  - children under 2 years of age
  - ask a doctor

Other information

- May cause staining. Use with caution when spraying near fabrics and unprotected surfaces.

Inactive ingredients

Citric Acid, Deionized Water, Disodium EDTA, Glycerin, Poloxamer 188, Polysorbate 20, SDA 40-B Alcohol

Principal Display Panel - 85 g Label

CVS HealthTM

Compare to the active ingredient in Cortaid®*

Instant Cooling Itch Relief Spray

Hydrocortisone, 1%

Intensive therapy

- Touchless application
- Covers the itch so it won't spread

NET WT 3 OZ (85 g)